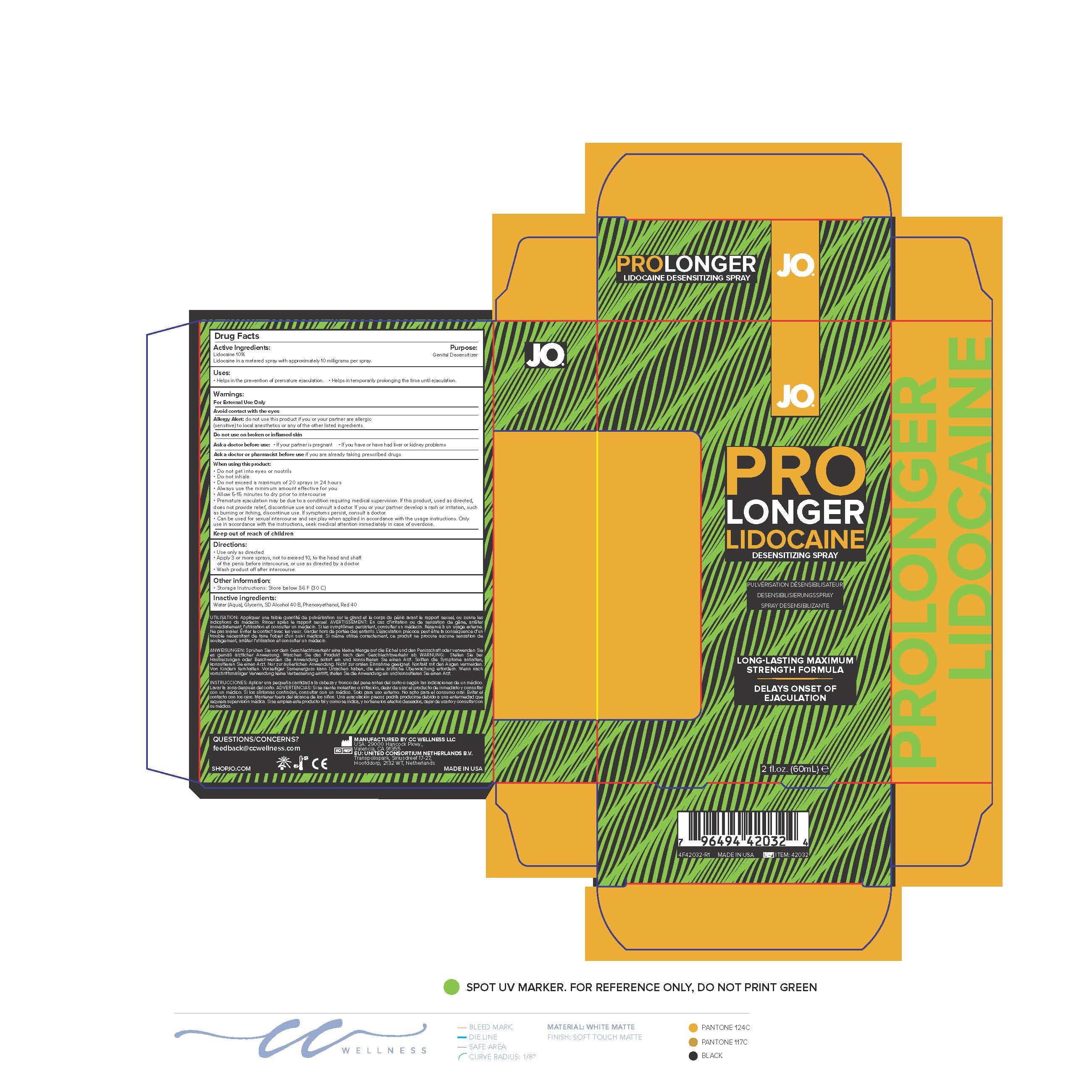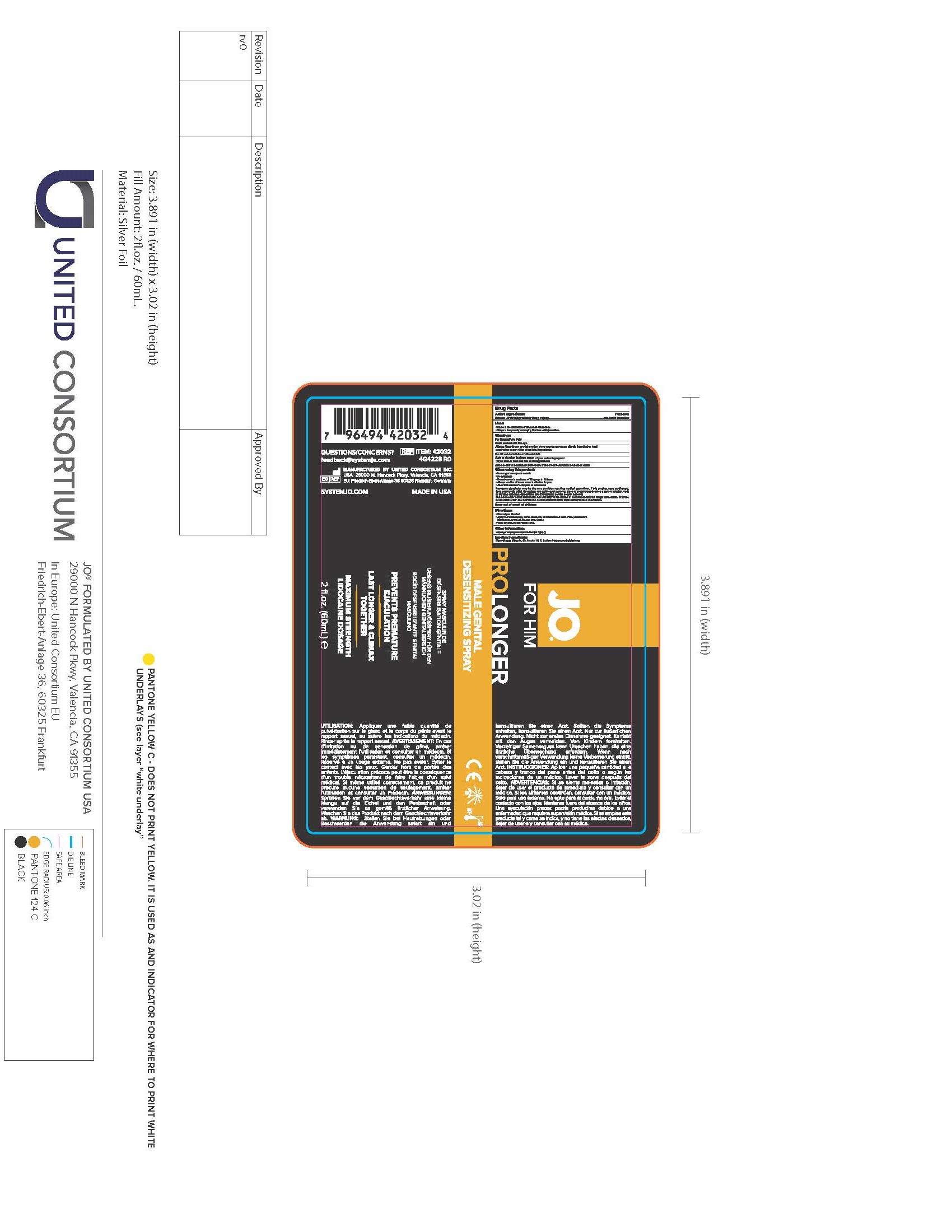 DRUG LABEL: JO for Him Prolonger with Lidocaine
NDC: 71683-001 | Form: SPRAY
Manufacturer: CC Wellness  LLC
Category: otc | Type: HUMAN OTC DRUG LABEL
Date: 20250912

ACTIVE INGREDIENTS: LIDOCAINE HYDROCHLORIDE 10 g/10 g
INACTIVE INGREDIENTS: GLYCERIN; PHENOXYETHANOL; WATER; TERT-BUTYL ALCOHOL; FD&C RED NO. 40

Active Ingredients:

Lidocaine USP(10%) (Approximately 10mg per Spray

Purpose:

Male Genital Desensitizer

Warnings:

For External Use Only

Avoid contact with the eye

Allergy Alert: do not use this product if you or your partner are allergic (sensitive) to local anesthetis or any other of the other listed ingredients.

Do not use on broken or inflamed skin

Ask a doctor before use:

If your partner is pregnant

If you have or have had liver or kidney problems

Ask a doctor or pharmacist before use

If you are already taking prescribed drugs

When using this product:

do not get into eys or nostrils

do not inhale

do not exceed a maximum of 20 sprays in 24 hours

Always use a minimum amount effective for you

allow 5-15 minutes to dry prior to intercourse

Premature ejaculation may be due to a condition requiring medical supervision. If this product, used as directed, does not provide relief, discontinue use and consult a doctor. If you or your partner develop a rash or irritation, such as burning or itching, discontinue use. If symptoms persist, consult a doctor. Can be used for sexual intercourse and sex play when applied in accordance with the useage instructions. Only use in accordance with the instructions, seek medical attention immediately in case of overdose.

Keep out of reach of children

Directions:

Use only as directed

Apply 3 or more sprays, not to exceed 10, to the head and shaft of the penis before intercourse, or use as directed by a doctor.

Wash product off after intercourse

Other information:

Storeage instructions: Store below 86 F (30 C)

Inactive ingredients:

Water (Aqua), Glycerin, SD Alcohol 40 B, Sodium Hydroxymethylglycinate

Directions:

Apply 3 or more sprays, not to exceed 10, to the head and shaft of the penis before intercourse, or use as directed by doctor..